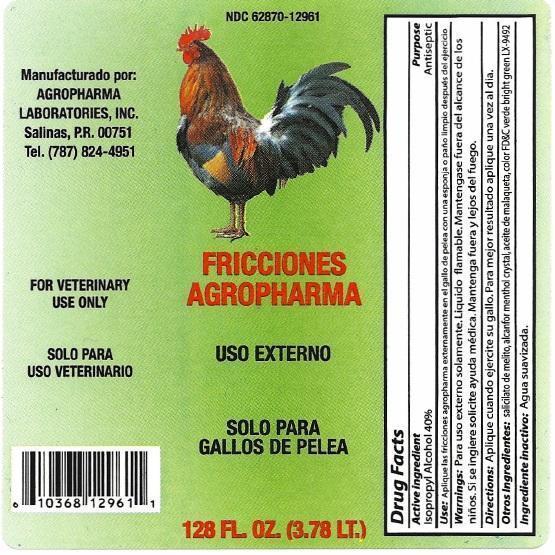 DRUG LABEL: Fricciones Agropharma
NDC: 62870-129 | Form: SOLUTION
Manufacturer: AGROPHARMA LABORATORIES INC
Category: animal | Type: OTC ANIMAL DRUG LABEL
Date: 20130917

ACTIVE INGREDIENTS: ISOPROPYL ALCOHOL 40 mL/100 mL
INACTIVE INGREDIENTS: WATER

Fricciones Agropharma

Active Ingrdients

ISOPROPYL ALCOHOL

Inactive Ingrdient Section

Water

Purpose

Antiseptic

Warnings and Precautions

For external use only. Flammable. Keep out the reach of children. If ingested call for medical help. Keep away from fire or flame.

FOR VETERINARY USE ONLY

Keep Out of Reach of Children

Keep out of reach children, in case of accedental ingestion, seek professional assistance or contact poision center immdietly.

Dosage and Administration

Apply when fighting cock is exercised,for best result apply once daily.

Indication and Usage

For antiseptic purpose.